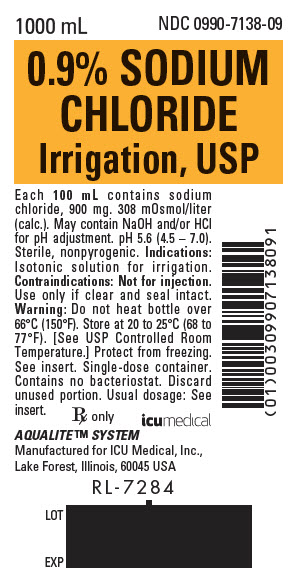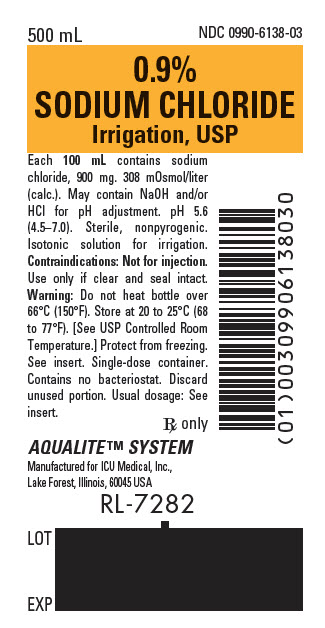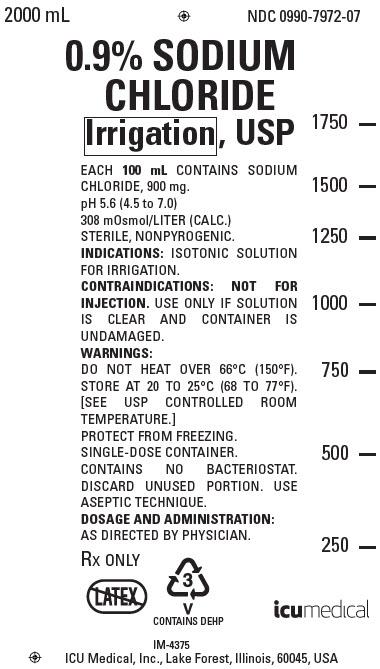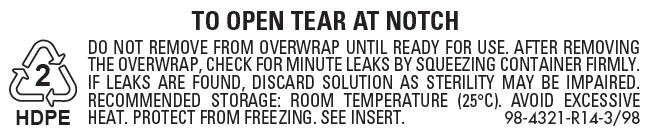 DRUG LABEL: Sodium Chloride
NDC: 0990-7138 | Form: IRRIGANT
Manufacturer: ICU Medical Inc.
Category: prescription | Type: HUMAN PRESCRIPTION DRUG LABEL
Date: 20201029

ACTIVE INGREDIENTS: SODIUM CHLORIDE 900 mg/100 mL
INACTIVE INGREDIENTS: WATER

0.9% SODIUM CHLORIDE IRRIGATION, USP

For All General Irrigation, Washing, Rinsing and Dilution Purposes

Not For Injection By Usual Parenteral Routes

Flexible Irrigation Container

Semi-rigid Irrigation Container

Rx only

DESCRIPTION

These products are sterile, nonpyrogenic solutions of electrolytes in water for injection intended only for sterile irrigation, washing, rinsing and dilution purposes.

Each 100 mL of 0.9% Sodium Chloride Irrigation, USP contains: Sodium chloride 900 mg; pH 5.6 (4.5 to 7.0). May contain sodium hydroxide and/or hydrochloric acid for pH adjustment. The solution is isotonic (308 mOsmol/liter, CALC.) and has the following electrolyte content (mEq/liter): Na^+ 154; Cl^− 154.

These irrigations contain no bacteriostat, antimicrobial agent or added buffer and are intended only for use as single-dose or short procedure irrigation. When smaller volumes are required the unused portion should be discarded.

Each of these irrigations may be classified as a sterile irrigant, wash, rinse, diluent and pharmaceutical vehicle.

Sodium Chloride, USP is chemically designated NaCl, a white crystalline powder freely soluble in water.

Water for Injection, USP is chemically designated H2O.

The flexible plastic container is fabricated from a specially formulated polyvinylchloride. Water can permeate from inside the container into the overwrap but not in amounts sufficient to affect the solution significantly.

The semi-rigid container is fabricated from a specially formulated polyolefin. It is a copolymer of ethylene and propylene. The container requires no vapor barrier to maintain the proper drug concentration.

Solutions in contact with the plastic container may leach out certain chemical components from the plastic in very small amounts; however, biological testing was supportive of the safety of the plastic container materials. Exposure to temperatures above 25°C/77°F during transport and storage will lead to minor losses in moisture content. Higher temperatures lead to greater losses. It is unlikely that these minor losses will lead to clinically significant changes within the expiration period.

CLINICAL PHARMACOLOGY

Each of these irrigation solutions exert a mechanical cleansing action for sterile irrigation of body cavities, tissues or wounds, indwelling urethral catheters and surgical drainage tubes and for washing, rinsing or soaking surgical dressings, instruments and laboratory specimens. Each also serves as a diluent or vehicle for drugs used for irrigation or other pharmaceutical preparations.

0.9% Sodium Chloride Irrigation, USP provides an isotonic saline irrigation identical in composition with 0.9% Sodium Chloride Injection, USP (normal saline).

0.9% Sodium Chloride Irrigation, USP is considered generally compatible with living tissues and organs.

Sodium chloride in water dissociates to provide sodium (Na^+) and chloride (Cl^−) ions. Sodium (Na^+) is the principal cation of the extracellular fluid and plays a large part in the therapy of fluid and electrolyte disturbances. Chloride (Cl^−) has an integral role in buffering action when oxygen and carbon dioxide exchange occurs in the red blood cells. The distribution and excretion of sodium (Na^+) and chloride (Cl^−) are largely under the control of the kidney which maintains a balance between intake and output.

Water is an essential constituent of all body tissues and accounts for approximately 70% of total body weight. Average normal adult daily requirement ranges from two to three liters (1.0 to 1.5 liters each for insensible water loss by perspiration and urine production).

Water balance is maintained by various regulatory mechanisms. Water distribution depends primarily on the concentration of electrolytes in the body compartments and sodium (Na^+) plays a major role in maintaining physiologic equilibrium.

INDICATIONS AND USAGE

Each of these solutions is indicated for all general irrigation, washing, rinsing and dilution purposes which permit use of a sterile, nonpyrogenic electrolyte solution.

CONTRAINDICATIONS

NOT FOR INJECTION BY USUAL PARENTERAL ROUTES.

An electrolyte solution should not be used for irrigation during electrosurgical procedures.

WARNINGS

FOR IRRIGATION ONLY. NOT FOR INJECTION.

Entry of a hypotonic solution into the circulation may cause hemolysis.

Irrigating fluids have been demonstrated to enter the systemic circulation in relatively large volumes; thus each of these irrigations must be regarded as a systemic drug. Absorption of large amounts can cause fluid and/or solute overloading resulting in dilution of serum electrolyte concentrations, overhydration, congested states or pulmonary edema.

The risk of dilutional states is inversely proportional to the electrolyte concentrations of administered parenteral solutions. The risk of solute overload causing congested states with peripheral and pulmonary edema is directly proportional to the electrolyte concentrations of such solutions.

Do not heat container over 66°C (150°F).

PRECAUTIONS

Do not use for irrigation that may result in absorption into the blood.

Caution should be observed when a hypotonic solution is used for continuous irrigation or allowed to "dwell" inside body cavities because of possible absorption into the blood stream and the production of intravascular hemolysis and circulatory overload.

Aseptic technique is essential with the use of sterile solutions for irrigation of body cavities, wounds and urethral catheters or for wetting dressings that come in contact with body tissues.

When used as a "pour" irrigation, no part of the contents should be allowed to contact the surface below the outer protected thread area of the semi-rigid wide mouth container. The flexible container is designed for use with nonvented irrigation sets. When used for irrigation via irrigation equipment, the administration set should be attached promptly. Unused portions should be discarded and a fresh container of appropriate size used for the start-up of each cycle or repeat procedure. For repeated irrigations of urethral catheters, a separate container should be used for each patient.

Do not administer unless solution is clear, seal is intact and container is undamaged.

Discard unused portion.

Carcinogenesis, Mutagenesis, Impairment of Fertility:

Studies with Sodium Chloride Irrigation, USP have not been performed to evaluate carcinogenic potential, mutagenic potential, or effects on fertility.

Nursing Mothers:

Caution should be exercised when Sodium Chloride Irrigation, USP is administered to a nursing woman.

Pregnancy:

Teratogenic Effects.

Pregnancy Category C. Animal reproduction studies have not been conducted with Sodium Chloride Irrigation, USP. It is also not known whether Sodium Chloride Irrigation, USP can cause fetal harm when administered to a pregnant woman or can affect reproduction capacity. Sodium Chloride Irrigation, USP should be given to a pregnant woman only if clearly needed.

Pediatric Use:

Safety and effectiveness of Sodium Chloride irrigation solution in pediatric patients have not been established by adequate and well-controlled trials. However, the use of Sodium Chloride irrigation solution in the pediatric population is referenced in the medical literature. The Warnings, Precautions, and Adverse Reactions identified in the label should be observed in the pediatric population.

Geriatric Use:

An evaluation of current literature revealed no clinical experience identifying differences in response between elderly and younger patients.

This drug is known to be substantially secreted by the kidney, and the risk of toxic reactions to this drug may be greater in patients with impaired renal function. Because elderly patients are more likely to have decreased renal function, care should be taken in dose selection, and it may be useful to monitor renal function.

ADVERSE REACTIONS

Possible adverse effects arising from the irrigation of body cavities, tissues, or indwelling catheters and tubes are usually avoidable when proper procedures are followed. Displaced catheters or drainage tubes can lead to irrigation or infiltration of unintended structures or cavities. Excessive volume or pressure during irrigation of closed cavities may cause undue distension or disruption of tissues. Accidental contamination from careless technique may transmit infection.

Should any adverse reaction occur, discontinue the irrigant, evaluate the patient, institute appropriate therapeutic countermeasures and save the remainder of the fluid for examination if deemed necessary.

OVERDOSAGE

In the event of overhydration or solute overload, re-evaluate the patient and institute appropriate corrective measures. See WARNINGS, PRECAUTIONS, and ADVERSE REACTIONS.

DOSAGE AND ADMINISTRATION

The dose is dependent upon the capacity or surface area of the structure to be irrigated and the nature of the procedure. When used as a diluent or vehicle for other drugs, the manufacturer's recommendations should be followed.

Drug Interactions

Additives may be incompatible. Consult with pharmacist, if available. When introducing additives, use aseptic technique, mix thoroughly and do not store.

Parenteral drug products should be inspected visually for particulate matter and discoloration prior to administration, whenever solution container permits. See PRECAUTIONS.

HOW SUPPLIED

0.9% Sodium Chloride Irrigation, USP:

Container Size | NDC
Single-dose 500 mL semi-rigid irrigation container | 0409-6138-03 [Manufactured for ICU Medical, Inc., Lake Forest, Illinois, 60045, USA]
Single-dose 500 mL semi-rigid irrigation container | 0990-6138-03
Single-dose 250 mL semi-rigid irrigation container | 0409-6138-22
Single-dose 250 mL semi-rigid irrigation container | 0990-6138-22
Single-dose 1000 mL semi-rigid irrigation container | 0409-7138-09
Single-dose 1000 mL semi-rigid irrigation container | 0990-7138-09
Single-dose 1500 mL semi-rigid irrigation container | 0409-7138-36
Single-dose 1500 mL semi-rigid irrigation container | 0990-7138-36
Single-dose 1000 mL flexible irrigation container | 0409-7972-05 [Manufactured by ICU Medical, Inc., Lake Forest, Illinois, 60045, USA]
Single-dose 1000 mL flexible irrigation container | 0990-7972-05
Single-dose 2000 mL flexible irrigation container | 0409-7972-07
Single-dose 2000 mL flexible irrigation container | 0990-7972-07

ICU Medical is transitioning NDC codes from "0409" to "0990" labeler code. Both NDC codes are expected to be in the market for a period of time.

Store at 20 to 25°C (68 to 77°F). [See USP Controlled Room Temperature.] Protect from freezing.

Revised: July, 2018

EN-4660

ICU Medical, Inc., Lake Forest, Illinois, 60045, USA

PRINCIPAL DISPLAY PANEL - 1000 mL Bottle Label

1000 mL
NDC 0990-7138-09

0.9% SODIUM
CHLORIDE
Irrigation, USP

Each 100 mL contains sodium
chloride, 900 mg. 308 mOsmol/liter
(calc.). May contain NaOH and/or HCl
for pH adjustment. pH 5.6 (4.5 – 7.0).
Sterile, nonpyrogenic. Indications:
Isotonic solution for irrigation.
Contraindications: Not for injection.
Use only if clear and seal intact.
Warning: Do not heat bottle over
66°C (150°F). Store at 20 to 25°C (68 to
77°F). [See USP Controlled Room
Temperature.] Protect from freezing.
See insert. Single-dose container.
Contains no bacteriostat. Discard
unused portion. Usual dosage: See
insert.

Rx only

icumedical

AQUALITE™ SYSTEM

Manufactured for ICU Medical, Inc.,
Lake Forest, Illinois, 60045 USA

RL-7284

LOT

EXP

PRINCIPAL DISPLAY PANEL - 500 mL Bottle Label

500 mL
NDC 0990-6138-03

0.9%
SODIUM CHLORIDE
Irrigation, USP

Each 100 mL contains sodium
chloride, 900 mg. 308 mOsmol/liter
(calc.). May contain NaOH and/or
HCl for pH adjustment. pH 5.6
(4.5–7.0). Sterile, nonpyrogenic.
Isotonic solution for irrigation.
Contraindications: Not for injection.
Use only if clear and seal intact.
Warning: Do not heat bottle over
66°C (150°F). Store at 20 to 25°C (68
to 77°F). [See USP Controlled Room
Temperature.] Protect from freezing.
See insert. Single-dose container.
Contains no bacteriostat. Discard
unused portion. Usual dosage: See
insert.

Rx only

AQUALITE™ SYSTEM

Manufactured for ICU Medical, Inc.,
Lake Forest, Illinois, 60045 USA

RL-7282

LOT

EXP

PRINCIPAL DISPLAY PANEL - 2000 mL Bag Label

2000 mL
NDC 0990-7972-07

0.9% SODIUM
CHLORIDE
Irrigation , USP

EACH 100 mL CONTAINS SODIUM
CHLORIDE, 900 mg.
pH 5.6 (4.5 to 7.0)
308 mOsmol/LITER (CALC.)
STERILE, NONPYROGENIC.
INDICATIONS: ISOTONIC SOLUTION
FOR IRRIGATION.
CONTRAINDICATIONS: NOT FOR
INJECTION. USE ONLY IF SOLUTION
IS CLEAR AND CONTAINER IS
UNDAMAGED.
WARNINGS:
DO NOT HEAT OVER 66°C (150°F).
STORE AT 20 TO 25°C (68 TO 77°F).
[SEE USP CONTROLLED ROOM
TEMPERATURE.]
PROTECT FROM FREEZING.
SINGLE-DOSE CONTAINER.
CONTAINS NO BACTERIOSTAT.
DISCARD UNUSED PORTION. USE
ASEPTIC TECHNIQUE.
DOSAGE AND ADMINISTRATION:
AS DIRECTED BY PHYSICIAN.

RX ONLY

3
V
CONTAINS DEHP

icumedical

IM-4375

ICU Medical, Inc., Lake Forest, Illinois, 60045, USA

PRINCIPAL DISPLAY PANEL - 2000 mL Bag Overwrap

TO OPEN TEAR AT NOTCH

2
HDPE

DO NOT REMOVE FROM OVERWRAP UNTIL READY FOR USE. AFTER REMOVING
THE OVERWRAP, CHECK FOR MINUTE LEAKS BY SQUEEZING CONTAINER FIRMLY.
IF LEAKS ARE FOUND, DISCARD SOLUTION AS STERILITY MAY BE IMPAIRED.
RECOMMENDED STORAGE: ROOM TEMPERATURE (25°C). AVOID EXCESSIVE
HEAT. PROTECT FROM FREEZING. SEE INSERT.
98-4321-R14-3/98